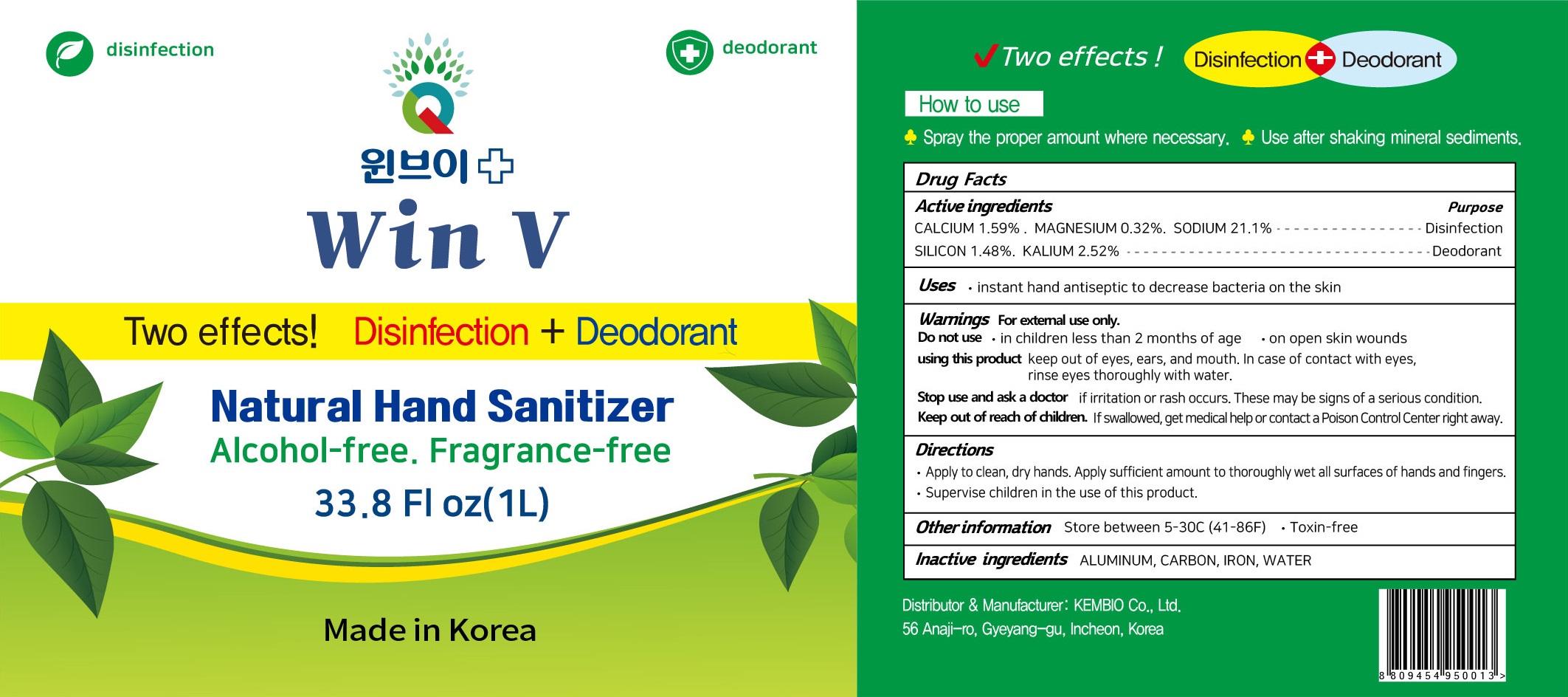 DRUG LABEL: Win V Natural Hand Sanitizer
NDC: 80403-010 | Form: SPRAY
Manufacturer: KEMBIO.CO.,LTD
Category: otc | Type: HUMAN OTC DRUG LABEL
Date: 20200923

ACTIVE INGREDIENTS: CALCIUM 1.59 g/100 mL; MAGNESIUM 0.32 g/100 mL; SODIUM 21.1 g/100 mL; SILICON 1.48 g/100 mL; DIPOTASSIUM ASPARTATE 2.52 g/100 mL
INACTIVE INGREDIENTS: ALUMINUM; ACTIVATED CHARCOAL; IRON; WATER

ACTIVE INGREDIENT

CALCIUM 1.59%
MAGNESIUM 0.32%
SODIUM 21.1%
SILICON 1.48%
KALIUM 2.52%

INACTIVE INGREDIENT SECTIONS

ALUMINUM, CARBON, IRON, WATER

PURPOSE

Disinfection, Deodorant

WARNINGS

For external use only.
--------------------------------------------------------------------------------------------------------
Do not use
• in children less than 2 months of age
• on open skin wounds
--------------------------------------------------------------------------------------------------------
When using this product keep out of eyes, ears, and mouth. In case of contact with eyes, rinse eyes thoroughly with water.
--------------------------------------------------------------------------------------------------------
Stop use and ask a doctor if irritation or rash occurs. These may be signs of a serious condition.
--------------------------------------------------------------------------------------------------------
Keep out of reach of children. If swallowed, get medical help or contact a Poison Control Center right away.

KEEP OUT OF REACH OF CHILDREN

If swallowed, get medical help or contact a Poison Control Center right away.

Uses

• instant hand antiseptic to decrease bacteria on the skin

Directions

• Apply to clean, dry hands. Apply sufficient amount to thoroughly wet all surfaces of hands and fingers. Rub onto hands until dry.
• Supervise children in the use of this product.

Other information

• Store between 5-30C (41-86F)
• Toxin-free